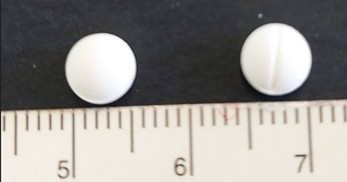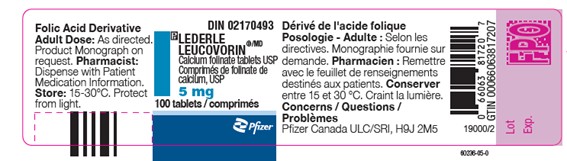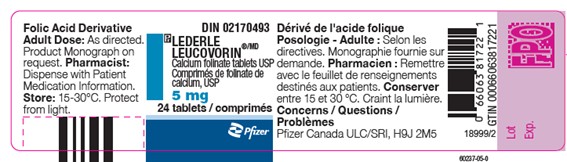 DRUG LABEL: LEDERLE LEUCOVORIN
NDC: 73591-5886 | Form: TABLET
Manufacturer: FARMASIERRA MANUFACTURING SL
Category: prescription | Type: HUMAN PRESCRIPTION DRUG LABEL
Date: 20251124

ACTIVE INGREDIENTS: LEUCOVORIN CALCIUM 5 mg/1 1

Lederle Leucovorin_"Unapproved drug for use in drug shortage"

Letter

URGENT: Important Prescribing Information Letter

Subject: Temporary Importation of Lederle Leucovorin®(Calcium Folinate tablets, USP) from Canada to Address U.S. Drug Shortage

December 2025

Dear Health Care Provider,

Due to the sho1tage of Leucovorin Calcium tablets, USP in the United States (U.S.) market, Pfizer is coordinating at the request of the U.S. Food and Drng Administration (FDA) to temporarily import unapproved Lederle Leucovorin®(Calcium Folinate tablets, USP) 5 mg tablets marketed in Canada.

This product is manufactured by Pfizer's Contract Manufacturer, FannasieITa, located in Madrid, Spain. The FDA has not approved Pfizer's Lederle Leucovorin (Calcium Folinate tablets USP), 5 mg tablets in the U.S.; however, the FDA is pennitting the tempora1y impo1tation and distribution of this product. Leucovorin Calcium tablets, USP, is refeITed to as Calcium Folinate tablets, USP, outside of the U.S.

Effective immediately, and during this temporaiy period, Pfizer will distribute the following presentation(s) of unapproved Lederle Leucovorin®(Calcium Folinate, USP):

Product: Lederle Leucovorin®, Calcium Folinate USP
Strength: 5 mg Tablet
Packaging: 1 × 24 Bottle
NDC: 0069-5886-24
Batch: X773
Expiration Date: 04-30-2026
Canada Marketing Authorization: DIN 02170493 / GTIN 066063817221
Product: Lederle Leucovorin®, Calcium Folinate USP
Strength: 5 mg Tablet
Packaging: 1 × 24 Bottle
NDC: 0069-5886-24
Batch: X830
Expiration Date: 10-31-2026
Canada Marketing Authorization: DIN 02170493 / GTIN 066063817221
Product: Lederle Leucovorin®, Calcium Folinate USP
Strength: 5 mg Tablet
Packaging: 1 × 24 Bottle
NDC: 0069-5886-24
Batch: Z361
Expiration Date: 03-31-2027
Canada Marketing Authorization: DIN 02170493 / GTIN 066063817221
Product: Lederle Leucovorin®, Calcium Folinate USP
Strength: 5 mg Tablet
Packaging: 1 × 100 Bottle
NDC: 0069-5886-99
Batch: X831
Expiration Date: 10-31-2026
Canada Marketing Authorization: DIN 02170493 / GTIN 066063817207
Product: Lederle Leucovorin®, Calcium Folinate USP
Strength: 5 mg Tablet
Packaging: 1 × 100 Bottle
NDC: 0069-5886-99
Batch: Z362
Expiration Date: 03-31-2027
Canada Marketing Authorization: DIN 02170493 / GTIN 066063817207

It is important to note that there are differences between the FDA-approved Leucovorin Calcium, USP products and the Calcium Folinate tablets, USP, marketed in Canada by Pfizer, Inc. Please see the product side-by-side label comparison table, where FDA-approved Leucovorin Calcium Tablets, USP 5 mg, manufactured by Teva Pharmaceuticals USA, Inc., is used as a reference.

It is important to note the following differences:

Lederle Leucovorin® (Calcium Folinate tablets, USP) 5 mg tablets is indicated for diminishing the toxicity and counteracting the effect of impaired methotrexate elimination. Treatment of megaloblastic anemias due to folate deficiency, as in sprue, nutritional deficiency, megaloblastic anemias of pregnancy and infancy. FDA-approved Leucovorin Calcium, USP, product is contraindicated for pernicious anemia and other megaloblastic anemias caused by vitamin B12 deficiency.
The container label will display the text used and approved for marketing Lederle Leucovorin® (Calcium Folinate tablets, USP) in Canada containing English and French text.
Health Canada has not authorized an indication for pediatric use for the imported product. FDA-approved Leucovorin Calcium, USP, includes a specific warning in the Drug Interactions section regarding folic acid which in large amounts may counteract the antiepileptic effect of phenobarbital, phenytoin and primidone, and increase the frequency of seizures in susceptible children. The Canadian Product Monograph does not mention this specific age group (10-12).
The Canadian Product Monograph includes a Post Marketing section addressing Adverse Drug Reactions, including that cases of Stevens-Johnson Syndrome (SJS) and Toxic Epidermal Necrolysis (TEN), some fatal, have been reported in patients receiving calcium folinate in combination with other agents known to be associated with these disorders. A contributory role of leucovorin in these occurrences of SJS/TEN cannot be excluded. Fatalities have occurred as a result of gastrointestinal toxicity (predominantly mucositis and diarrhea) and myelosuppression. In patients with diarrhea, rapid clinical deterioration leading to death can occur.
The barcode of the imported product label may not register accurately on the U.S. scanning systems. Institutions should manually input the important product information into their systems and confirm that the barcode, if scanned, provides correct information. Alternative procedures should be followed to assure that the correct drug product is being used and administered to individual patients.
The packaging of the imported product does not include serialization information. Pfizer’s Calcium Folinate, USP, marketed in Canada, does not meet the Drug Supply Chain Security (DSCSA) standards for Interoperable Exchange of Information for Tracing of Human, Finished Prescription Drugs. FDA has created an exemption for the product due to the shortage.
Leucovorin Calcium tablet, USP is available only by prescription in the U.S. However, the imported product does not have the statement “Rx only” on the labeling.

Please refer to the package inse1i for the FDA approved Leucovorin Calcium, USP, full Prescribing fufonnation.

Adverse Events and Product Quality Complaints

To repo1i adverse reactions or quality issues, contact Pfizer at 1-800-438-1985.

Adverse reactions or quality problems experienced with the use of this product may be repo1ied to the FDA's MedWatch Adverse Event Repo1iing Program either online, by regular mail, or by fax:

Complete and submit the repo1i Online: www.fda.gov/medwatch/repo1t.htm
Regular mail or Fax: download f01m www.fda.gov/MedWatch/getfonns.htm or call 1-800-332-1088 to request a repo1iing fonn, then complete and return to the address on the pre-addressed f01m, or submit by fax to 1-800-FDA-0l 78 (1-800-332-0178)
When repo1iing, please indicate product is Lederle Leucovorin from Pfizer Canada and provide the lot number

Contact Information

Please contact Pfizer Customer Service at 1-800-533-4535 or dropships@pfizer.com (Mon.-Fri. 8am-5:30pm ET) or your Pfizer representative for any questions you may have regarding this notification.

Sincerely,

Pfizer fuc.

Caleb Haii

US PAVE Business Unit Lead

Lederle Leucovorin 24 tablets

Lederle Leucovorin 100 tablets